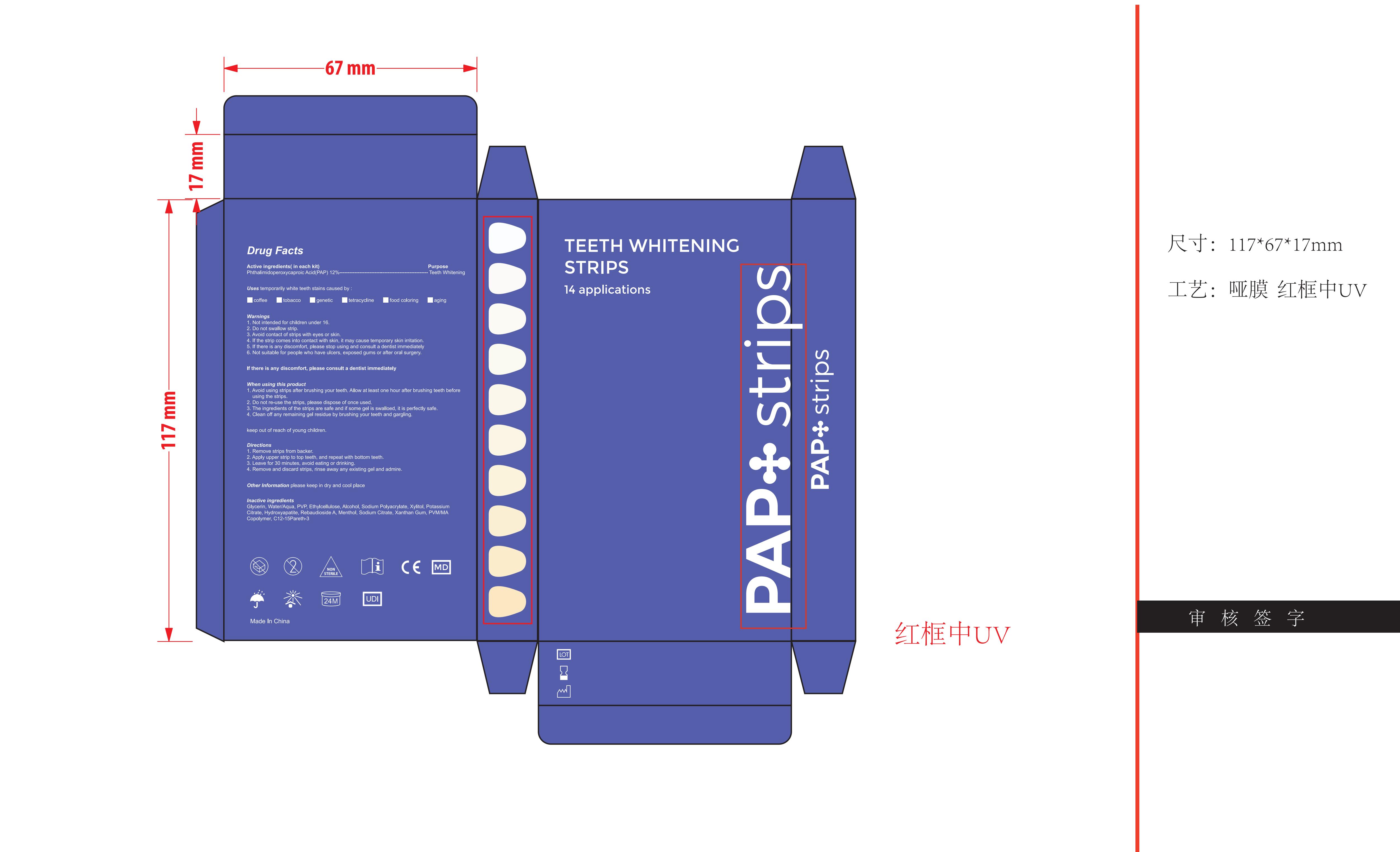 DRUG LABEL: Teeth Whitening Strips
NDC: 83812-004 | Form: PATCH
Manufacturer: LLRN PERSONAL CARE(SHENZHEN)CO., LTD
Category: otc | Type: HUMAN OTC DRUG LABEL
Date: 20231123

ACTIVE INGREDIENTS: PHTHALIMIDOPEROXYCAPROIC ACID 12 g/100 1
INACTIVE INGREDIENTS: POTASSIUM CITRATE; MENTHOL; XANTHAN GUM; WATER; ETHYLCELLULOSES; XYLITOL; REBAUDIOSIDE A; METHYL VINYL ETHER AND MALEIC ANHYDRIDE COPOLYMER (1100000 WAMW); ALCOHOL; SODIUM CITRATE; POVIDONE; TRIBASIC CALCIUM PHOSPHATE; C12-15 PARETH-3; SODIUM POLYACRYLATE (2500000 MW); GLYCERIN

Active Ingredient

Phthalimidoperoxycaproic Acid(PAP) 12%

Purpose

Teeth Whitening

Use

Teeth stains from coffee, tobacco, genetic, tetracycline, food coloring, aging and other factors that may cause discoloration.

Warnings

1. Not intended for children under 16.
2. Do not swallow strip.
3. Avoid contact of strips with eyes or skin.
4. If the strip comes into contact with skin, it may cause temporary skin irritation.
5. If there is any discomfort, please stop using and consult a dentist immediately
6. Not suitable for people who have ulcers, exposed gums or after oral surgery.

Do not use

Not intended for children under 16.
Not suitable for people who have ulcers, exposed gums or after oral surgery.

When Using

1. Avoid using strips after brushing your teeth. Allow at least one hour after brushing teeth before using the strips.
2. Do not re-use the strips, please dispose of once used.
3. The ingredients of the strips are safe and if some gel is swalloed, it is perfectly safe.
4. Clean off any remaining gel residue by brushing your teeth and gargling.

Stop Use

If there is any discomfort, please stop using.

Ask Doctor

If there is any discomfort, please consult a dentist immediately

Keep Oot Of Reach Of Children

keep out of reach of young children

Directions

1. Remove strips from backer.
2. Apply upper strip to top teeth, and repeat with bottom teeth.
3. Leave for 30 minutes, avoid eating or drinking.
4. Remove and discard strips, rinse away any existing gel and admire.

Other information

please keep in dry and cool place

Inactive ingredients

Glycerin、Water/Aqua、PVP、Ethylcellulose、Alcohol、Sodium Polyacrylate、Xylitol、Potassium Citrate、Hydroxyapatite、Rebaudioside A 、Menthol、Sodium Citrate、Xanthan Gum、PVM/MA Copolymer、C12-15Pareth-3